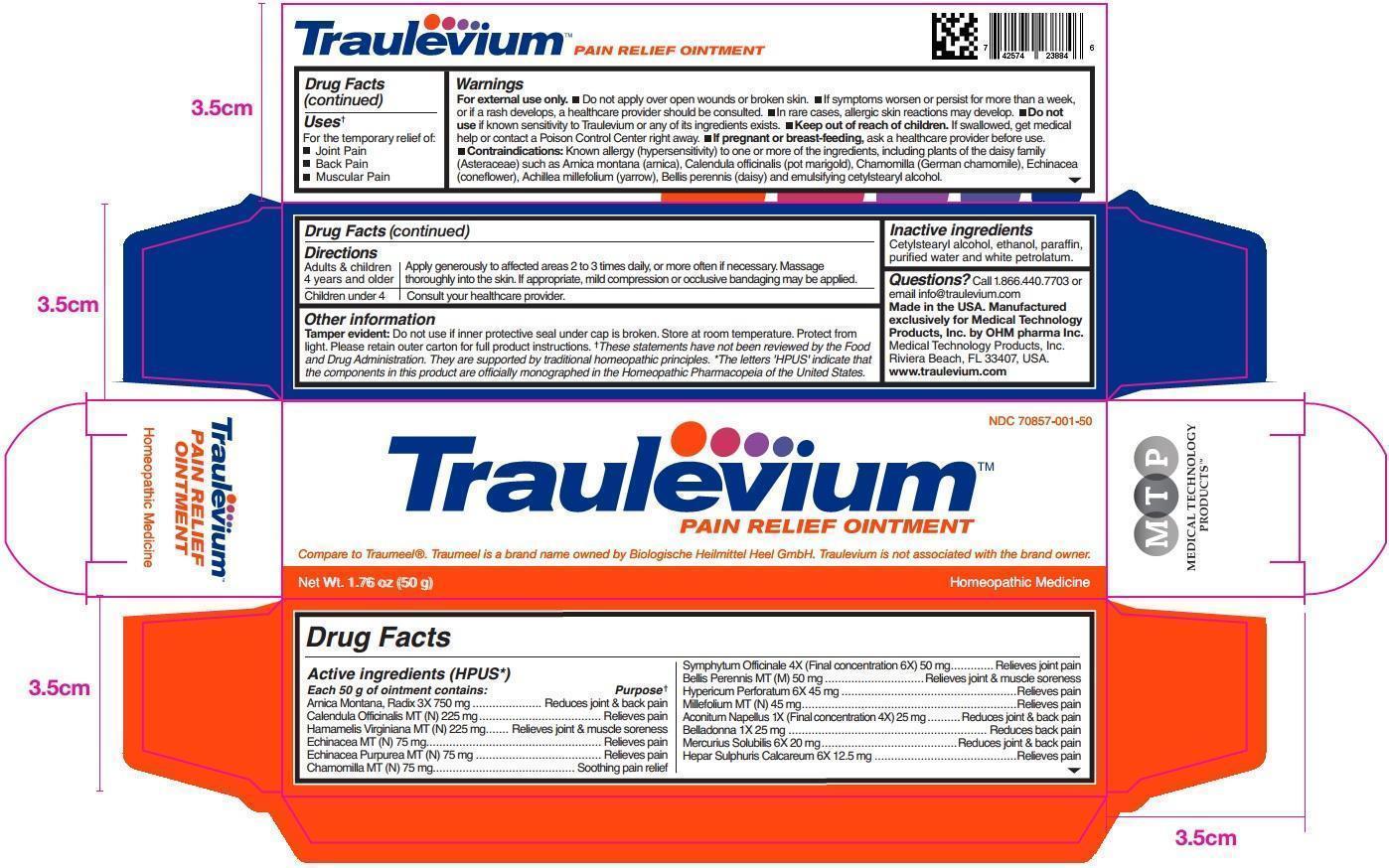 DRUG LABEL: Traulevium
NDC: 70857-001 | Form: OINTMENT
Manufacturer: Medical Technology Products, Inc.
Category: homeopathic | Type: HUMAN OTC DRUG LABEL
Date: 20211229

ACTIVE INGREDIENTS: ARNICA MONTANA ROOT 3 [hp_X]/50 g; CALENDULA OFFICINALIS FLOWERING TOP 225 mg/50 g; HAMAMELIS VIRGINIANA ROOT BARK/STEM BARK 225 mg/50 g; ECHINACEA, UNSPECIFIED 75 mg/50 g; ECHINACEA PURPUREA 75 mg/50 g; MATRICARIA RECUTITA 75 mg/50 g; COMFREY ROOT 6 [hp_X]/50 g; BELLIS PERENNIS 50 mg/50 g; HYPERICUM PERFORATUM 6 [hp_X]/50 g; ACHILLEA MILLEFOLIUM 45 mg/50 g; ACONITUM NAPELLUS 4 [hp_X]/50 g; ATROPA BELLADONNA 1 [hp_X]/50 g; MERCURIUS SOLUBILIS 6 [hp_X]/50 g; CALCIUM SULFIDE 6 [hp_X]/50 g
INACTIVE INGREDIENTS: WATER; ALCOHOL; PETROLATUM; PARAFFIN; CETOSTEARYL ALCOHOL

Traulevium Pain Relief Ointment

ACTIVE INGREDIENTS

Active ingredients (HPUS*) | Purpose**
Each 50 g of ointment contains:
Arnica Montana, Radix 3X 750 mg | Reduces joint & back pain
Calendula Officinalis MT (N) 225 mg | Relieves pain
Hamamelis Virginiana MT (N) 225 mg | Relieves joint & muscle soreness
Echinacea MT (N) 75 mg | Relieves pain
Echinacea Purpurea MT (N) 75 mg | Relieves pain
Chamomilla MT (N) 75 mg | Soothing pain relief
Symphytum Officinale 4X (Final concentration 6X) 50 mg | Relieves joint pain
Bellis Perennis MT (M) 50 mg | Relieves joint & muscle soreness
Hypericum Perforatum 6X 45 mg | Relieves pain
Millefolium MT (N) 45 mg | Relieves pain
Aconitum Napellus 1X (Final concentration 4X) 25 mg | Reduces joint & back pain
Belladonna 1X 25 mg | Reduces back pain
Mercurius Solubilis 6X 20 mg | Reduces joint & back pain
Hepar Sulphuris Calcareum 6X 12.5 mg | Relieves pain

USES

Uses** For the temporary relief of:

- Joint Pain
- Back Pain
- Muscular Pain

WARNINGS

For external use only.

- Do not apply over open wounds or broken skin.
- If symptoms worsen or persist for more than a week, or if a rash develops, a healthcare provider should be consulted.
- In rare cases, allergic skin reactions may develop.
- Do not use if known sensitivity to Traulevium or any of its ingredients exists.
- Keep out of reach of children. If swallowed, get medical help or contact a Poison Control Center right away.
- If pregnant or breast-feeding, consult a healthcare provider before use.
- Contraindications: Known allergy (hypersensitivity) to one of the ingredients, including plants of the daisy family (Asteraceae) such as Arnica montana (arnica), Calendula officinalis (pot marigold), Chamomilla (German chamomile), Echinacea (coneflower), Achillea millefolium (yarrow), Bellis perennis (daisy) and emulsifying cetylstearyl alcohol.

Keep out of the reach of children.

DIRECTIONS

Adults and children 4 years and older | Apply generously to affected areas 2 to 3 times daily, or more often if necessary. Massage thoroughly into the skin. If appropriate, mild compression or occlusive bandaging may be applied.
Children under 4 | Consult your healthcare provider.

OTHER INFORMATION

Tamper evident: Do not use if protective seal under cap is broken. Store at room temperature. Protect from light. Please retain outer carton for full product instructions.

**These statements have not been reviewed by the Food and Drug Administration. They are supported by traditional homeopathic principles.

*The letters 'HPUS' indicate that the components in this product are officially monographed in the Homeopathic Pharmacopeia of the United States.

INACTIVE INGREDIENTS

Cetylstearyl alcohol, ethanol, paraffin, purified water and white petrolatum.

QUESTIONS?

Call 1.866.440.7703 or e-mail info@traulevium.com

Made in the USA.

Manufactured exclusively for Medical Technology Products, Inc. by OHM pharma Inc.

Medical Technology Products, Inc.

Riviera Beach, FL 33407, USA.

www.traulevium.com

PACKAGE LABELING

NDC 70857-001-50

Traulevium™

Pain Relief Ointment

Homeopathic Medicine

Compare to Traumeel®. Traumeel is a brand name owned by Biologische Heilmittel Heel GmbH. Traulevium is not associated with the brand owner.

Net Wt. 1.76 oz (50 g)

PURPOSE

Pain Relief Ointment